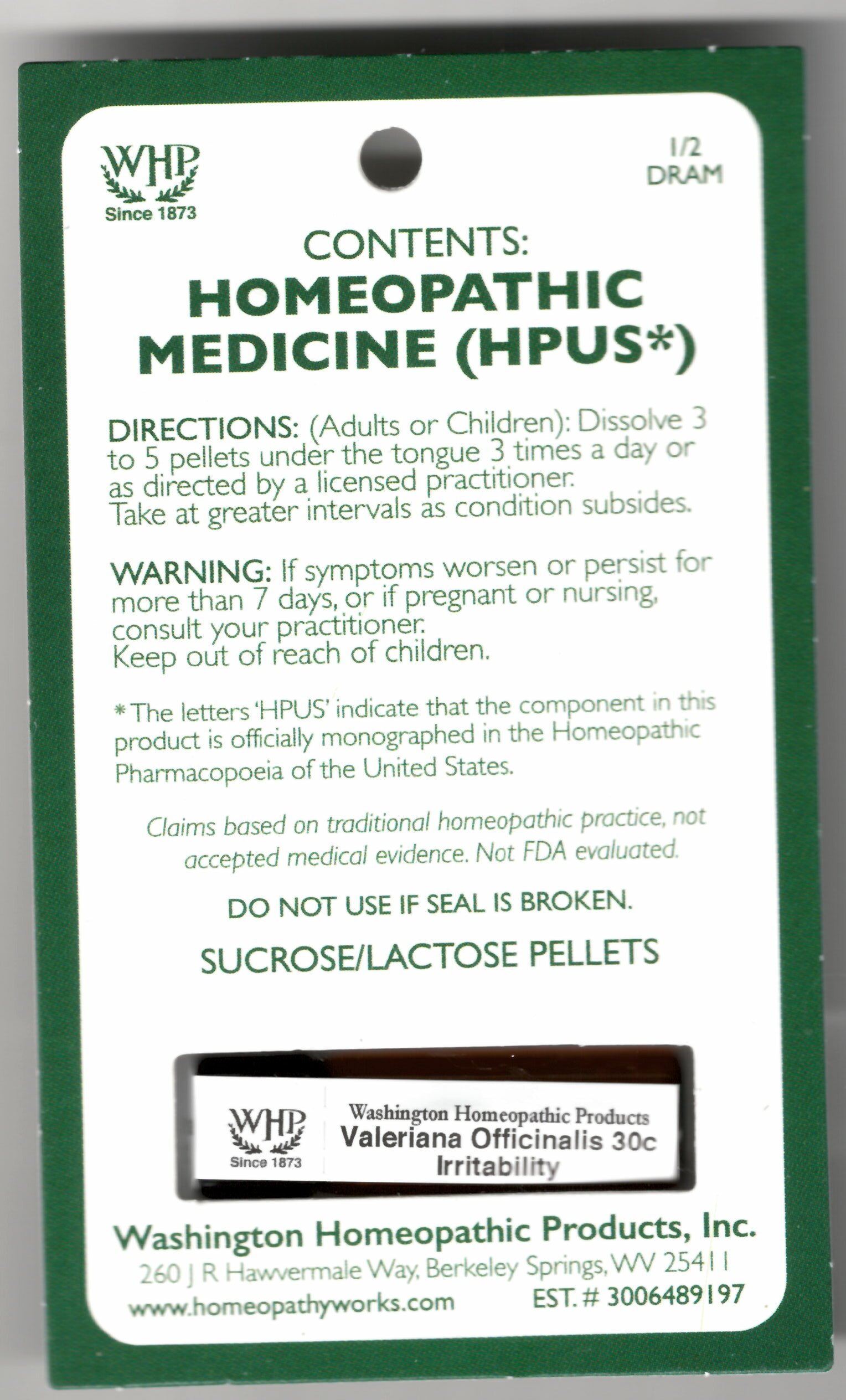 DRUG LABEL: Valeriana Officinalis Kit Refill
NDC: 71919-758 | Form: PELLET
Manufacturer: Washington Homeopathic Products
Category: homeopathic | Type: HUMAN OTC DRUG LABEL
Date: 20250128

ACTIVE INGREDIENTS: VALERIAN 200 [hp_C]/1 1
INACTIVE INGREDIENTS: SUCROSE; LACTOSE

Valeriana Officinalis Kit Refill

ACTIVE INGREDIENTS

VALERIANA OFFICINALIS 30C

USES

To relieve the symptoms of hysteria.

KEEP OUT OF REACH OF CHILDREN

Keep this and all medicines out of reach of children.

INDICATIONS

VALERIANA OFFICINALIS Hysteria

STOP USE AND ASK DOCTOR

If symptoms persist/worsen or if pregnant/nursing, stop use and consult your practitioner.

DIRECTIONS

Adults: Dissolve 3 to 5 under the tongue three times a day or as directed by Lic. Practitioner. Take at greater intervals as condition subsides.

Children: Dissolve 3 to 5 under the tongue three times a day or as directed by Lic. Practitioner. Take at greater intervals as condition subsides.

INACTIVE INGREDIENTS

Sucrose/Lactose